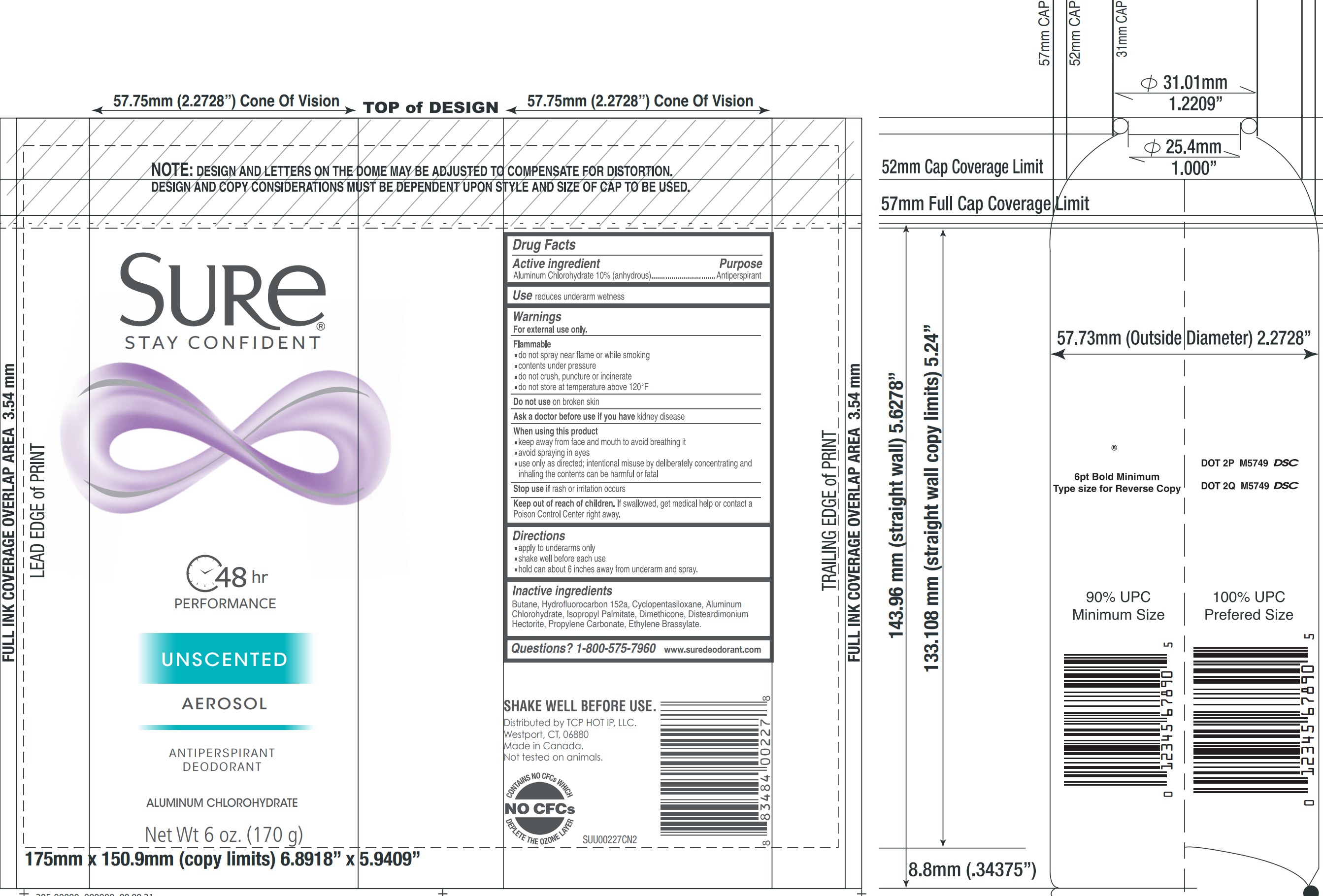 DRUG LABEL: Sure Unscented Antiperspirant and Deodorant
NDC: 81277-007 | Form: AEROSOL, SPRAY
Manufacturer: Sodalis USA LLC
Category: otc | Type: HUMAN OTC DRUG LABEL
Date: 20241108

ACTIVE INGREDIENTS: ALUMINUM CHLOROHYDRATE ANHYDROUS 10 g/100 g
INACTIVE INGREDIENTS: BUTANE; 1,1-DIFLUOROETHANE; CYCLOMETHICONE 5; ISOPROPYL PALMITATE; DIMETHICONE; DISTEARDIMONIUM HECTORITE; PROPYLENE CARBONATE; ETHYLENE BRASSYLATE

Sure Unscented Aerosol Antiperspirant and Deodorant

Active ingredient

Aluminum Chlorohydrate 10% (anhydrous)

Purpose

Antiperspirant

Use

reduces underarm wetness

Warnings

For external use only.

Flammable

- do not spray near flame or while smoking
- contents under pressure
- do not crush, puncture or incinerate
- do not store at temperature above 120ºF

Do not use

on broken skin

Ask a doctor before use if you have

kidney disease

When using this product

- keep away from face and mouth to avoid breathing it
- avoid spraying in eyes
- use only as directed; intentional misuse by deliberately concentrating and inhaling the contents can be harmful or fatal

Stop use if

rash or irritation occurs

Keep out of reach of children.

If swallowed, get medical help or contact a Poison Control Center right away.

Directions

- apply to underarms only
- shake well before each use
- hold can about 6 inches away from underarm and spray.

Inactive ingredients

Butane, Hydrofluorocarbon 152a, Cyclopentasiloxane, Aluminum Chlorohydrate, Isopropyl Palmitate, Dimethicone, Disteardimonium Hectorite, Propylene Carbonate, Ethylene Brassylate.

Questions?

1-800-575-7960 www.suredeodorant.com